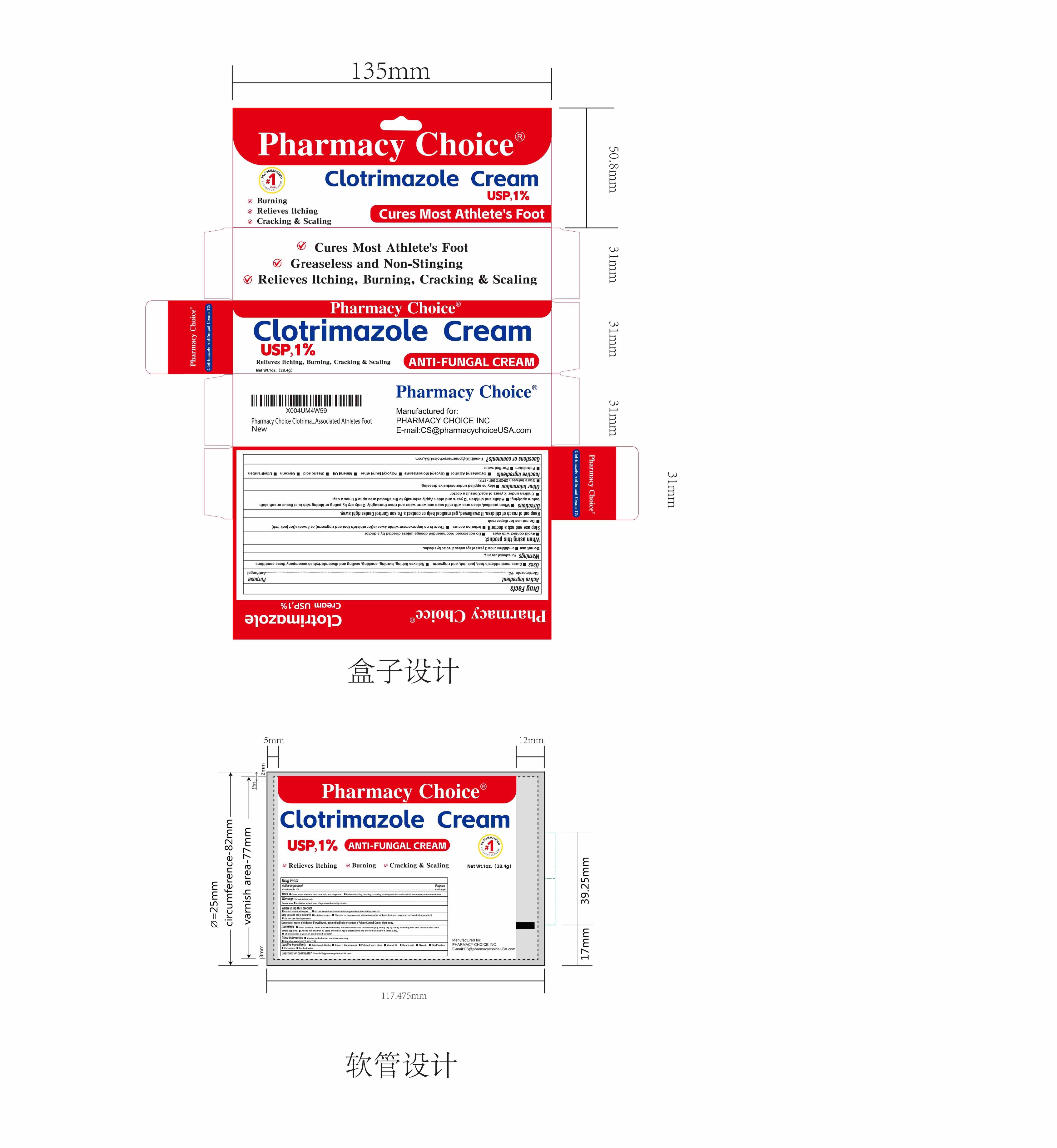 DRUG LABEL: CLOTRIMAZOLE 1%
NDC: 87228-1010 | Form: CREAM
Manufacturer: PHARMACY CHOICE INC
Category: otc | Type: HUMAN OTC DRUG LABEL
Date: 20260208

ACTIVE INGREDIENTS: CLOTRIMAZOLE 10 mg/1 g
INACTIVE INGREDIENTS: WATER; PETROLATUM; STEARIC ACID; GLYCERIN; GLYCERYL MONOSTEARATE; CETOSTEARYL ALCOHOL; MINERAL OIL; ETHYLPARABEN

Active Ingredient

Clotrimazole 1%

Purpose

Antifungal

Uses

cures most athlete's foot, jock itch and ringworm
relieves itching, burning, cracking, scaling and discomfort which accompany these conditions

Directions

When practical, clean area with mild soap and warm water and rinse thoroughly. Geny dry by pating or bloting with toiet tissue or soft clotibefore applying. Adults and children 12 years and older: Apply externally to the affected area up to 6 times a day.
Chidren under i2 years of age:Consult a doctor

Warnings

For external use only

Do not use on children under 2 years of age unless directed by a doctor.

When using this product

avoid contact with eyes.

Stop use and ask a doctor if

irritation occurs
there is no improvement within 4 weeks (for athlete's foot or ringworm) or 2 weeks (for jock itch).

Do not use for diaper rash

Keep out of reach of children

If swallowed, get medical help or contact a Poison Control Center right away.

Other information

store between 20° - 25°C (68° - 77°F)
see carton or tube crimp for lot number and expiration date

Inactive ingredients

Cetostearyl Alcohol, Glyceryl Monostearate,Polyoxyl lauryl ether, Mineral Oil, Stearic acid, Glycerin EthylParaben, Petrolatum, Purified water

DOSAGE AND ADMINISTRATION

1